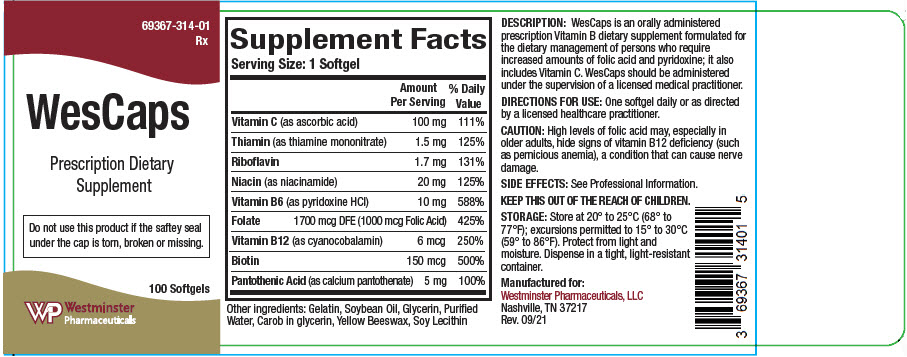 DRUG LABEL: WesCaps
NDC: 69367-314 | Form: CAPSULE, GELATIN COATED
Manufacturer: Westminster Pharmaceuticals, LLC
Category: other | Type: DIETARY SUPPLEMENT
Date: 20211216

ACTIVE INGREDIENTS: ASCORBIC ACID 100 mg/1 1; THIAMINE MONONITRATE 1.5 mg/1 1; RIBOFLAVIN 1.7 mg/1 1; NIACINAMIDE 20 mg/1 1; PYRIDOXINE HYDROCHLORIDE 10 mg/1 1; FOLIC ACID 1 mg/1 1; CYANOCOBALAMIN 6 ug/1 1; BIOTIN 150 ug/1 1; CALCIUM PANTOTHENATE 5 mg/1 1
INACTIVE INGREDIENTS: SOYBEAN OIL; GELATIN, UNSPECIFIED; GLYCERIN; WATER; LECITHIN, SOYBEAN

WesCaps

HEALTH CLAIM

69367-314-01
Rx

Prescription Dietary Supplement

DESCRIPTION

WesCaps is an orally administered prescription Vitamin B dietary supplement formulated for the dietary management of persons who require increases amounts of folic acid and pyridoxine; it also includes vitamin C. WesCaps should be administered under the supervision of a licensed medical practitioner.

STATEMENT OF IDENTITY

Supplement Facts
Serving Size: 1 Softgel
 | Amount Per Serving | % Daily Value
Vitamin C (as ascorbic acid) | 100 mg | 111%
Thiamin (as thiamine mononitrate) | 1.5 mg | 125%
Riboflavin | 1.7 mg | 131%
Niacin (as niacinamide) | 20 mg | 125%
Vitamin B6 (as pyridoxine HCl) | 10 mg | 588%
Folate | 1700 mcg DFE (1000 mcg Folic Acid) | 425%
Vitamin B12 (as cyanocobalamin) | 6 mcg | 250%
Biotin | 150 mcg | 500%
Pantothenic Acid (as calcium pantothenate) | 5 mg | 100%

Other ingredients: Gelatin, Soybean Oil, Glycerin, Purified Water, Carob in glycerin, Yellow Beeswax, Soy Lecithin

Side Effects

Allergic reactions have been reported following the use of oral folate.

Mild transient diarrhea, polycythemia vera, itching, transitory exanthema and the feeling of swelling of the entire body has been associated with cobalamin.

Paresthesia, somnolence, nausea, and headaches have been reported with pyridoxine.

KEEP THIS PRODUCT OUT OF THE REACH OF CHILDREN.

INTERACTIONS

Drugs which may interact with folate include but are not limited to:

- First generation anticonvulsants (folate may reduce their effectiveness)
- Capecitabine (folate may enhance its toxicity)
- Fluorouracil (folate may enhance its toxicity)

Drugs that may interfere with folate metabolism include, but are not limited to:

- Dihydrofolate Reductase Inhibitors
- Fluoxetine
- Nonsteroidal Anti-inflammatory Drugs
- Sulfasalazine
- Warfarin

Drugs which may interfere with the absorption of folate from the gastrointestinal tract or decrease plasma levels include, but are not limited to:

- Cholestyramine
- Colestipol
- Colchicine
- Levodopa
- Cycloserine
- Isotretinoin
- Oral Contraceptives
- Methylprednisolone
- Pancreatic Enzymes
- Pentamidine
- Smoking and Alcohol
- Sulfasalazine
- Metformin

Drugs which may interact with vitamin B6 include, but are not limited to:

- Levodopa (the action of levodopa may be antagonized by vitamin B6.)

Drugs which may interact with vitamin B12 include, but are not limited to:

- Antibiotics, cholestyramine, colchicine, colestipol, metformin, para-aminosalicylic acid, and potassium chloride (may decrease the absorption of vitamin B12)
- Nitrous oxide (can produce a functional vitamin B12 deficiency)

CONTRAINDICTIONS

This product is contraindicated in patients with a known hypersensitivity to any of its components.

CAUTION

High levels of folic acid may, especially in older adults, hide signs of vitamin B12 deficiency (such as pernicious anemia), a condition that can cause nerve damage.

PREGNANCY and NURSING MOTHERS

This product contains only B and C vitamins and is not intended for use as a prenatal/postnatal multivitamin.

DIRECTIONS FOR USE

One softgel daily or as directed by a licensed medical practitioner.

STORAGE

Store at 20° to 25°C (68° to 77°F); excursions permitted to 15° to 30°C (59° to 86°F). Protect from light and moisture. Dispense in a tight, light-resistant container.

HOW SUPPLIED

WesCaps is supplied as oval, black softgels imprinted on one side with "314" dispensed in child-resistant bottles of 100 softgels

69367-314-01

HEALTH CLAIM

KEEP THIS OUT OF REACH OF CHILDREN

All prescriptions using this product shall be pursuant to state statutes as applicable. This is not an Orange Book product.

Call your medical practitioner about side effects. You may report side effects by calling Westminster at 1-844-221-7294.

HEALTH CLAIM

Rx
Manufactured for:
Westminster Pharmaceuticals, LLC
Nashville, TN 37217
Rev. 09/21

PRINCIPAL DISPLAY PANEL - 100 Softgel Bottle Label

69367-314-01
Rx

WesCaps

Prescription Dietary
Supplement

Do not use this product if the saftey seal
under the cap is torn, broken or missing.

100 Softgels

Westminster
Pharmaceuticals